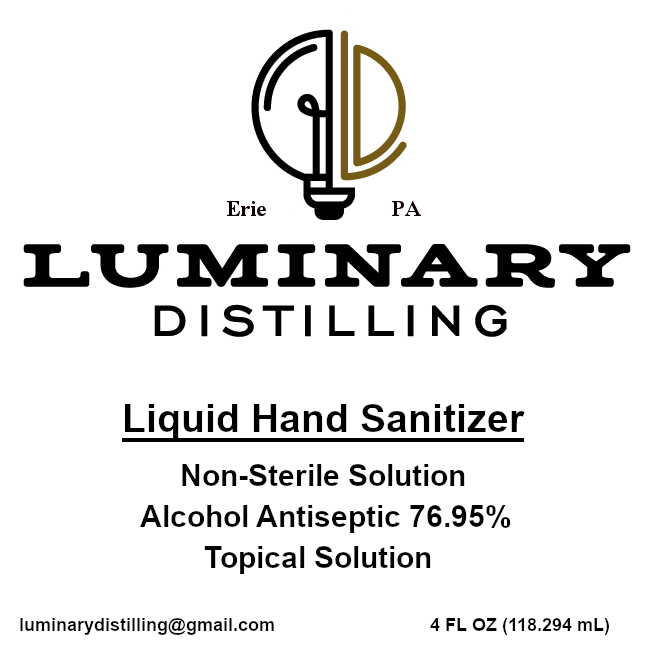 DRUG LABEL: Hand Sanitizer
NDC: 73888-101 | Form: LIQUID
Manufacturer: Luminary Distilling, LLC
Category: otc | Type: HUMAN OTC DRUG LABEL
Date: 20200328

ACTIVE INGREDIENTS: ALCOHOL 72 mL/100 mL
INACTIVE INGREDIENTS: GLYCERIN 1.875 mL/100 mL; HYDROGEN PEROXIDE 0.15 mL/100 mL; WATER 21.025 mL/100 mL; ISOPROPYL ALCOHOL 4.95 mL/100 mL

Warnings

For external use only. Flammable. Keep away from heat or flame

Active ingredients

Active ingredient[s] Purpose

Alcohol 76.95% Antiseptic

Do not use

* in children less than 2 months of age

* on open skin wounds

When using this product keep out of eyes, ears, and mouth. In case of contact with eyes, rinse eyes thoroughly with water.

Stop use and ask a doctor if irritation or rash occurs. These may be signs of a serious condition.

Keep out of reach of children. If swallowed, get medical help or contact a Poison Control Center right away.

Inactive ingredients

Inactive ingredients purified water USP (21.025%), isopropyl alcohol (4.95%), glycerin (1.875%), hydrogen peroxide (0.15%)

Other information

* Store between 15-30C (59-86F)

* Avoid freezing and excessive heat above 40C (104F)

Use[s]

Hand Sanitizer to help reduce bacteria that potentially can cause disease. For use when soap and water are not available.

Directions

* Place enough product on hands to cover all surfaces. Rub hands together until dry.

* Supervise children under 6 years of age when using this product to avoid swallowing.

Purpose

Antiseptic

Luminary Distilling Liquid Hand Sanitizer

Liquid Hand Sanitizer

Non-Sterile Solution

Alcohol Antiseptic 76.95%

Topical Solution